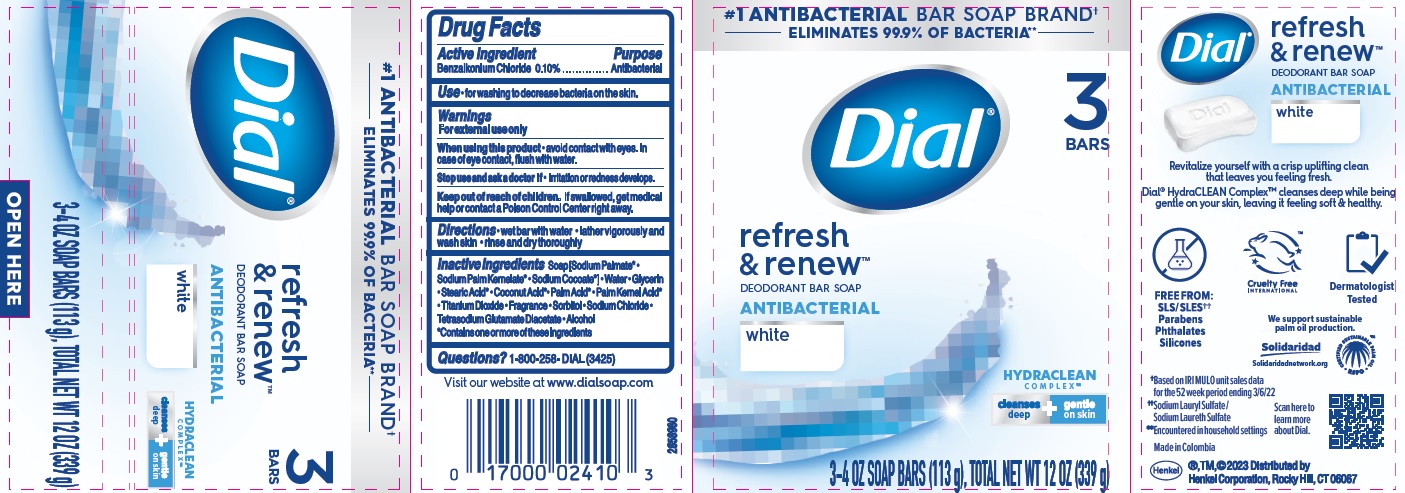 DRUG LABEL: Dial refresh and renew
NDC: 54340-260 | Form: SOAP
Manufacturer: Henkel Corporation
Category: otc | Type: HUMAN OTC DRUG LABEL
Date: 20250101

ACTIVE INGREDIENTS: BENZALKONIUM CHLORIDE 0.1 g/100 g
INACTIVE INGREDIENTS: SODIUM PALMATE; SODIUM COCOATE; COCONUT ACID; STEARIC ACID; SORBITOL; TETRASODIUM GLUTAMATE DIACETATE; PALM ACID; GLYCERIN; WATER; PALM KERNEL ACID; ALCOHOL; TITANIUM DIOXIDE; SODIUM CHLORIDE; SODIUM PALM KERNELATE

Dial refresh & renew antibacterial (White)

Drug Facts

Active ingredient

Benzalkonium Chloride 0.10%

Purpose

Antibacterial

INDICATIONS AND USAGE

Use • for washing to decrease bacteria on the skin

Warnings

For external use only

When using this product • avoid contact with the eyes. In case of eye contact, flush with water.

Stop use and ask a doctor if • irritation and redness develops.

Keep out of reach of children. If swallowed, get medical help or contact a Poison Control Center right away.

DOSAGE AND ADMINISTRATION

Directions • wet bar with water • lather vigorously and wash skin • rinse and dry thoroughly

INACTIVE INGREDIENT

Inactive ingredients Soap (Sodium Palmate* • Sodium Palm Kernelate* • Sodium Cocoate*) • Water • Glycerin • Stearic Acid* • Coconut Acid* • Palm Acid* • Palm Kernel Acid* • Titanium Dioxide • Fragrance • Sorbitol • Sodium Chloride • Tetrasodium Glutamate Diacetate • Alcohol

*Contains one or more of these ingredients

Questions? 1-800-258-DIAL (3425)

Visit our website at www.dialsoap.com

Henkel®, TM, ©2021 Distributed by

Henkel Corporation, Rocky Hill, CT 06067

Made in Columbia

PACKAGE LABEL

Dial® refresh & renew™

Antibacterial white

DEODORANT BAR SOAP

ELIMINATES 99% OF BACTERIA**

3-4 OZ SOAP BARS (113 g) EACH, TOTAL NET WT 12 OZ (339 g)